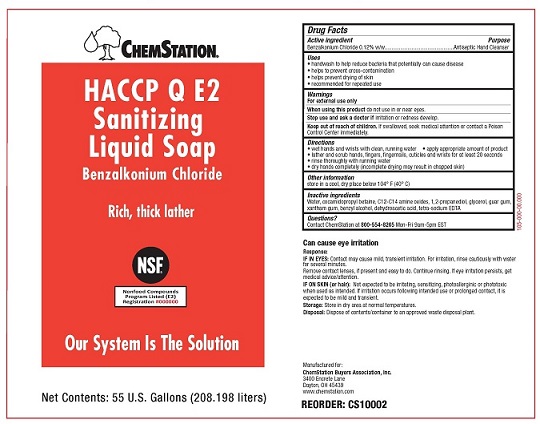 DRUG LABEL: Chemstation HACCP Q E2
NDC: 71212-101 | Form: LIQUID
Manufacturer: ChemStation
Category: otc | Type: HUMAN OTC DRUG LABEL
Date: 20250109

ACTIVE INGREDIENTS: BENZALKONIUM CHLORIDE 1.2 g/1 L
INACTIVE INGREDIENTS: XANTHAN GUM; BENZYL ALCOHOL; EDETATE SODIUM; DEHYDROACETIC ACID; PROPANEDIOL; GLYCERIN; COCAMIDOPROPYL BETAINE; (C10-C16)ALKYLDIMETHYLAMINE OXIDE; GUAR GUM; WATER

ChemStation HACCP Q E2 Sanitizing Liquid Soap

Drug Facts

Active Ingredient

Benzalkonium Chloride 0.12% w/w

Purpose

Antiseptic Hand Cleanser

Uses

- handwash to help reduce bacteria that potentially can cause disease
- helps to prevent cross contamination
- helps prevent drying of skin
- recommended for repeated use

Warnings

For external use only

WHEN USING

When using this productdo not use in or near eyes.

Stop use and ask a doctor ifirritation or redness develop.

Keep out of reach of children.If swallowed, seek medical attention or contact a Poison Control Center immediately.

Directions

- wet hands and wrists with clean, running water
- apply appropriate amount of product
- lather and scrub hands, fingers, fingernails, cuticles and wrists for at least 20 seconds
- rinse thoroughly with running water
- dry hands completely (incomplete drying may result in chapped skin)

Other Information

store in a cool, dry place below 104° F (40° C)

Inactive ingredients

Water, cocamidopropyl betaine, C12-14 amine oxides, 1,2 propanediol, glycerol, guar gum, xantham gum, benzyl alcohol, dehydroacetic acid, tetra-sodium EDTA

Questions?

Contact ChemStation at 800-554-8265Mon-Fri 9am-5pm EST

OTHER SAFETY INFORMATION

Can cause eye irritation

Response:

IF IN EYES:Contact may cause mild, transient irritation. For irritation, rinse cautiously with water for several minutes.

Remove contact lenses, if present and easy to do. Continue rinsing. If eye irritation persists, get medical advice/attention.

IF ON SKIN (or hair):Not expected to be irritating, sensitizing, photoallerginic or phototoxic when used as intended. If irritation occurs following intended use or prolonged contact, it is expected to be mild and transient.

Storage:Store in a dry area at normal temperatures.

Disposal:Dispose of contents/container to an approved waste disposal plant.

Manufactured for:

ChemStation Buyers Association, Inc.

3400 Encrete Lane

Dayton, OH 45439

www.chemstation.com

PACKAGE LABEL

CHEMSTATION®

HACCP Q E2 Sanitizing Liquid Soap

Benzalkonium Chloride

Rich, thick lather

Our System Is The Solution

Net Contents: 55 U.S. Gallons (208.198 liters)